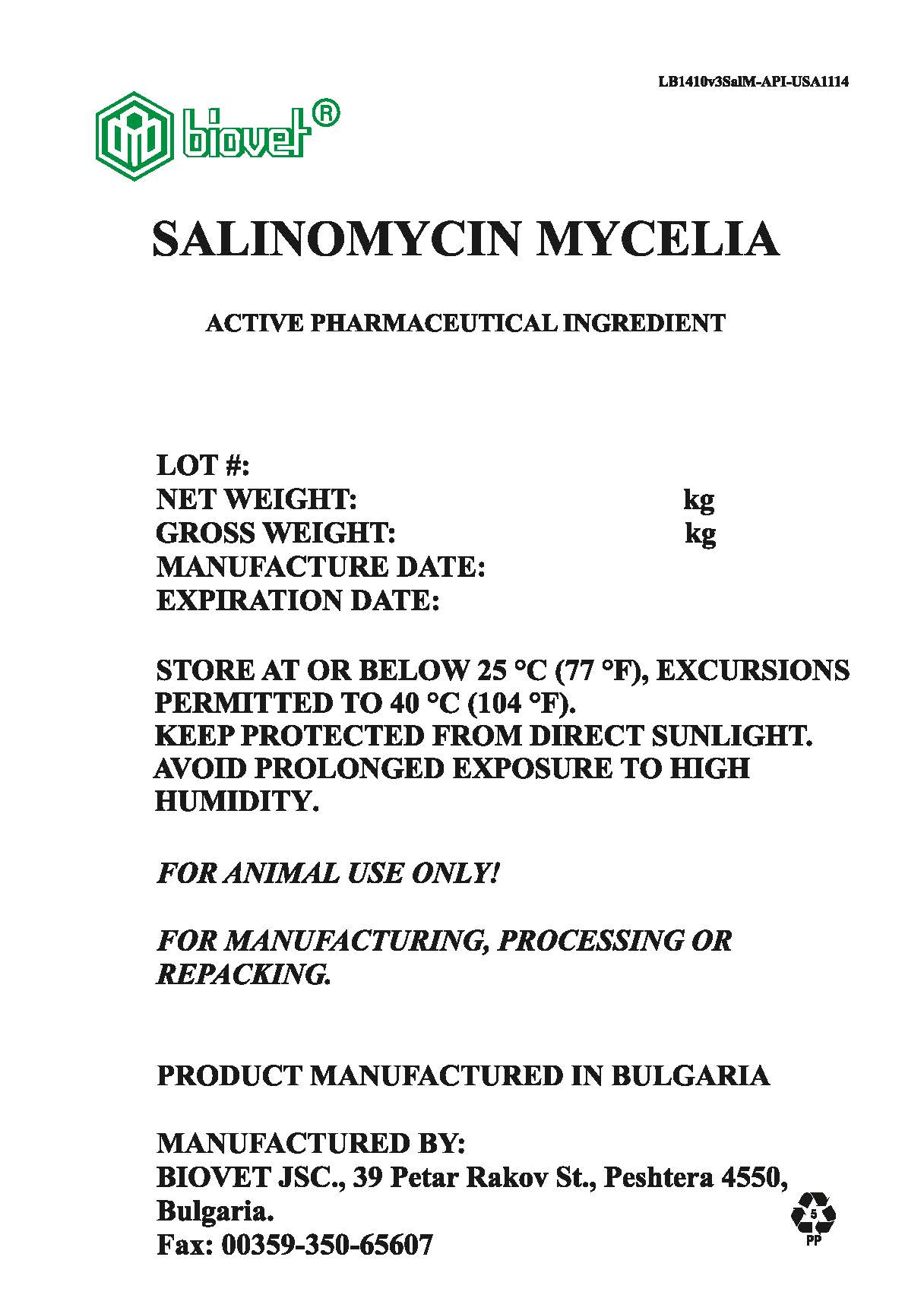 DRUG LABEL: Salinomycin Mycelia
NDC: 11311-889 | Form: Powder
Manufacturer: Biovet Joint Stock Company
Category: other | Type: BULK INGREDIENT - ANIMAL DRUG
Date: 20200730

ACTIVE INGREDIENTS: SALINOMYCIN .02 kg/.02 kg

Salinomycin Mycelia